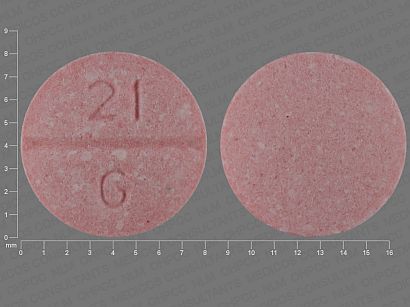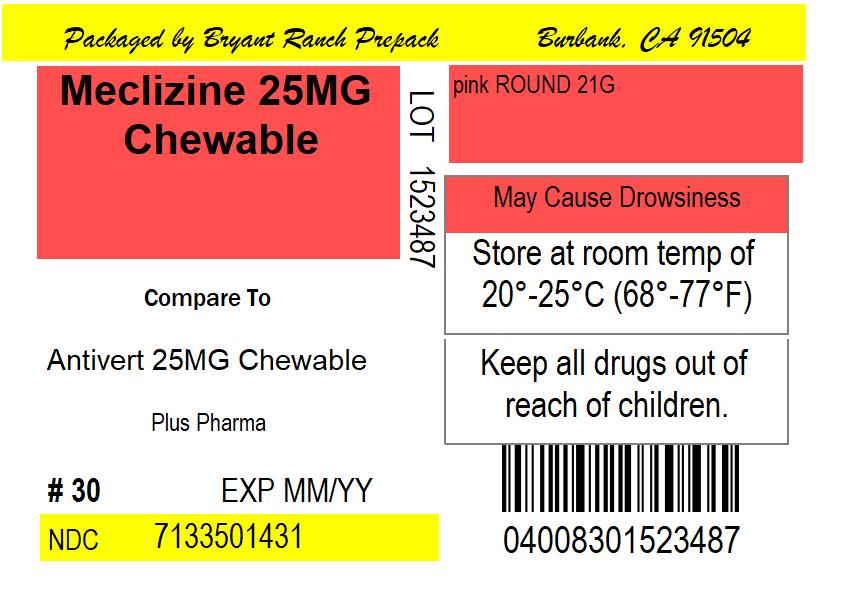 DRUG LABEL: Meclizine HCl 25 mg
NDC: 71335-0143 | Form: TABLET, CHEWABLE
Manufacturer: Bryant Ranch Prepack
Category: otc | Type: HUMAN OTC DRUG LABEL
Date: 20220209

ACTIVE INGREDIENTS: MECLIZINE HYDROCHLORIDE 25 mg/1 1
INACTIVE INGREDIENTS: ASPARTAME; SUCROSE; CROSCARMELLOSE SODIUM; DEXTROSE, UNSPECIFIED FORM; FD&C RED NO. 40; MAGNESIUM STEARATE; MALTODEXTRIN; MICROCRYSTALLINE CELLULOSE; SILICON DIOXIDE; SODIUM SULFATE; TRICALCIUM PHOSPHATE

Meclizine HCl 25 mg Chewable Tablets

DO NOT USE IF IMPRINTED SAFETY SEAL UNDER CAP IS BROKEN OR MISSING

Drug Facts

Active ingredient (in each chewable tablet)

Meclizine HCl, USP 25 mg

Purpose

Antiemetic

Uses

prevents and treats nausea, vomiting or dizziness due to motion sickness

Warnings

Do not use in children under 12 years of age unless directed by a doctor.

Ask a doctor before use if you have

- glaucoma
- a breathing problem such as emphysema or chronic bronchitis
- trouble urinating due to an enlarged prostate gland

Ask a doctor or pharmacist before use if you are taking sedatives or tranquilizers.

When using this product

- may cause drowsiness
- alcohol, sedatives and tranquilizers may increase drowsiness
- avoid alcoholic drinks
- use caution when driving a motor vehicle or operating machinery

PREGNANCY OR BREAST FEEDING

If pregnant or breast-feeding, ask a health professional before use

Keep out of reach of children.

In case of overdose, get medical help or contact the poison control center immediately.

Directions

- dosage should be taken one hour before travel starts.
- adults and children 12 years of age and older: Chew 1-2 tablets once daily or as directed by a doctor
- children under 12 years: do not give this product to children under 12 years of age unless directed by a doctor

Other information

- phenylketonurics: contains phenylalanine 0.28 mg per tablet
- store at room temperature in a dry place

INACTIVE INGREDIENT

Inactive ingredients Aspartame, croscarmellose sodium, dextrose, FD&C red #40 lake, magnesium stearate, maltodextrin, microcrystalline cellulose, natural and artificial flavors, silicon dioxide, sodium sulfate, sugar, tricalcium phosphate.

QUESTIONS

Questions? If you have any questions or comments or to report an adverse event, please contact (800) 795-9775.

Distributed by: Plus Pharma, Commack, NY 11725

*Plus Pharma is not affiliated with the owner of the registered trademark Bonine®.

HOW SUPPLIED

NDC: 71335-0143-1: 30 Tablets in a BOTTLE

NDC: 71335-0143-2: 20 Tablets in a BOTTLE

NDC: 71335-0143-3: 25 Tablets in a BOTTLE

NDC: 71335-0143-4: 40 Tablets in a BOTTLE

NDC: 71335-0143-5: 60 Tablets in a BOTTLE

NDC: 71335-0143-6: 90 Tablets in a BOTTLE

NDC: 71335-0143-7: 8 Tablets in a BOTTLE

NDC: 71335-0143-8: 14 Tablets in a BOTTLE

NDC: 71335-0143-9: 10 Tablets in a BOTTLE

NDC: 71335-0143-0: 120 Tablets in a BOTTLE

PACKAGE LABEL

Meclizine 25MG Chewable